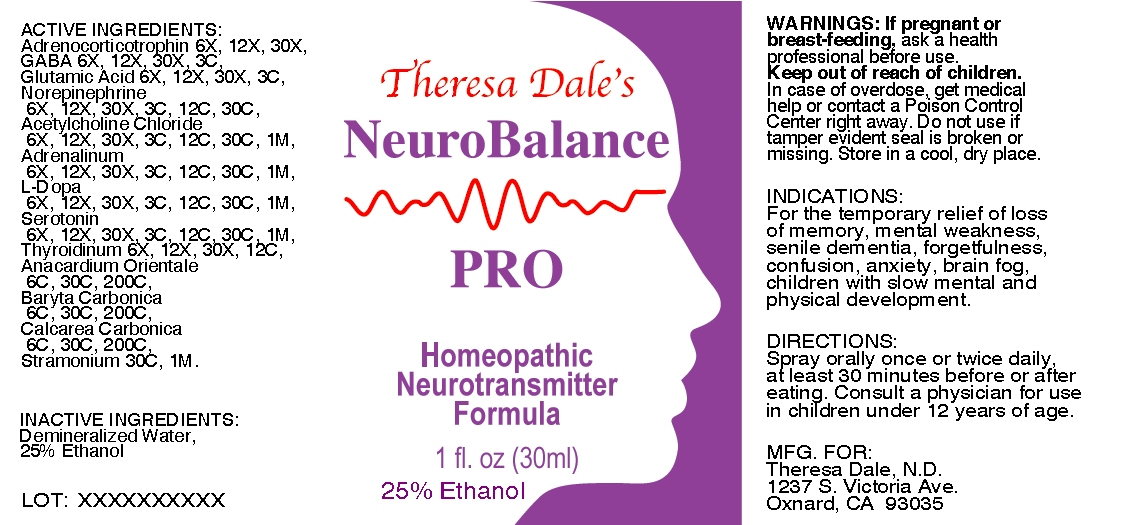 DRUG LABEL: Neuro Balance Pro
NDC: 57520-0144 | Form: SPRAY
Manufacturer: ApothecaCompany
Category: homeopathic | Type: HUMAN OTC DRUG LABEL
Date: 20100709

ACTIVE INGREDIENTS: CORTICOTROPIN 30 [hp_X]/1 mL; .GAMMA.-AMINOBUTYRIC ACID 3 [hp_C]/1 mL; GLUTAMIC ACID 3 [hp_C]/1 mL; NOREPINEPHRINE 30 [hp_C]/1 mL; ACETYLCHOLINE CHLORIDE 1 [hp_M]/1 mL; EPINEPHRINE 1 [hp_M]/1 mL; SEROTONIN 1 [hp_M]/1 mL; THYROID 12 [hp_C]/1 mL; BARIUM CARBONATE 200 [hp_C]/1 mL; OYSTER SHELL CALCIUM CARBONATE, CRUDE 200 [hp_C]/1 mL; DATURA STRAMONIUM 1 [hp_M]/1 mL; SEMECARPUS ANACARDIUM JUICE 200 [hp_C]/1 mL; LEVODOPA 1 [hp_M]/1 mL
INACTIVE INGREDIENTS: WATER; ALCOHOL

Neuro Balance Pro

ACTIVE INGREDIENT

ACTIVE INGREDIENTS: Adrenocorticotrophin 6X, 12X, 30X, GABA 6X, 12X, 30X, 3C, Glutamic Acid 6X, 12X, 30X, 3C, Norepinephrine 6X, 12X, 30X, 3C, 12C, 30C, Acetylcholine Chloride 6X, 12X, 30X, 3C, 12C, 30C, 1M, Adrenalinum 6X, 12X, 30X, 3C, 12C, 30C, 1M, L-Dopa 6X, 12X, 30X, 3C, 12C, 30C, 1M, Serotonin 6X, 12X, 30X, 3C, 12C, 30C, 1M, Thyroidinum 6X, 12X, 30X, 12C, Anacardium Orientale 6C, 30C, 200C, Baryta Carbonica 6C, 30C, 200C, Calcarea Carbonica 6C, 30C, 200C, Stramonium 30C, 1M.

PURPOSE

INDICATIONS: For the temporary relief of loss of memory, mental weakness, senile dementia, forgetfulness, confusion, anxiety, brain fog, children with slow mental and physical development.

WARNINGS

WARNINGS: If pregnant or breast-feeding, ask a health professional before use.

Keep out of reach of Children. In case of overdose, get medical help or contact a Poison Control Center right away.

Do not use if tamper evident seal is broken or missing.

Store in a cool, dry place.

DOSAGE AND ADMINISTRATION

DIRECTIONS: Spray orally once or twice daily, at least 30 minutes before or after eating. Consult a physician for use in children under 12 years of age.

INACTIVE INGREDIENTS: Demineralized Water, 25% Ethanol

QUESTIONS

MFG FOR:

Theresa Dale, N. D.

1237 S. Victoria Ave.

Oxnard, CA 93035

PACKAGE LABEL

Theresa Dale's

NEURO BALANCE

PRO

HOMEOPATHIC NEUROTRANSMITTER FORMULA

1 FL OZ (30 ML)